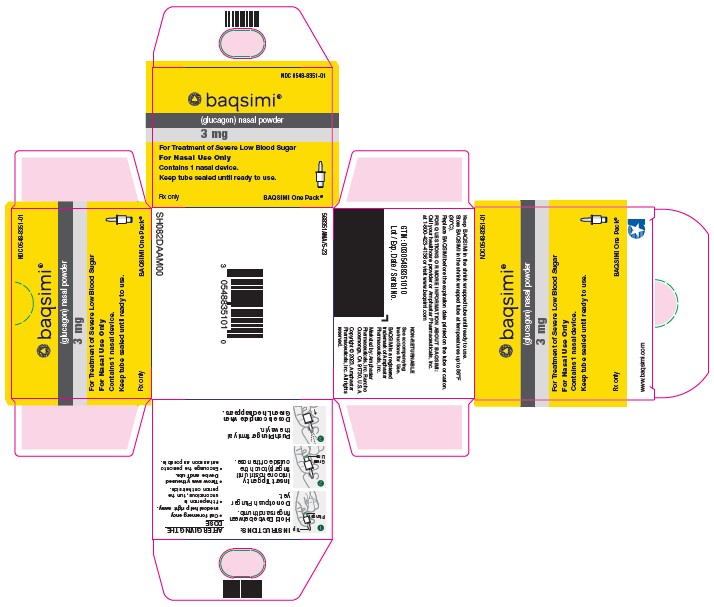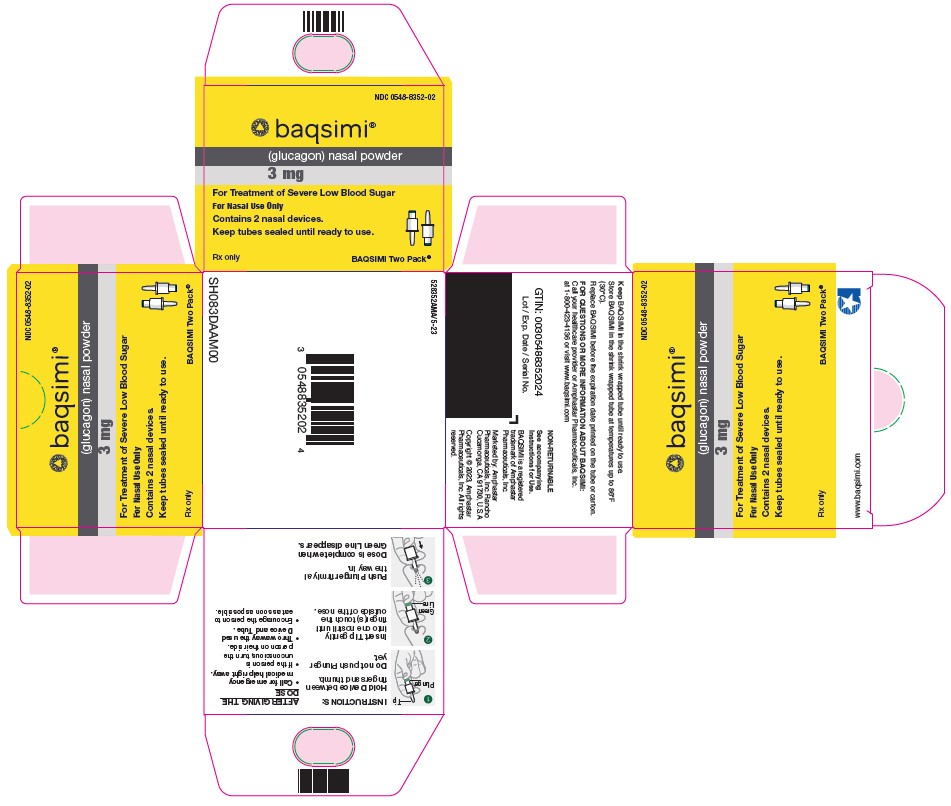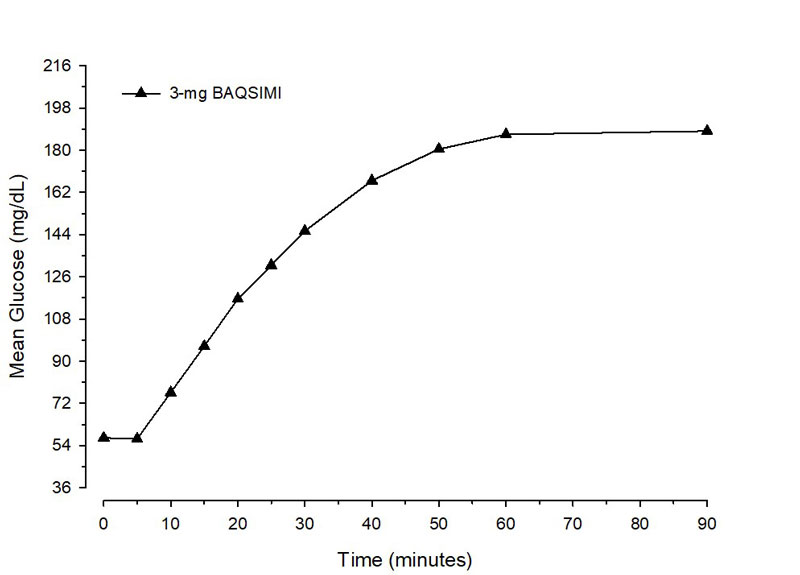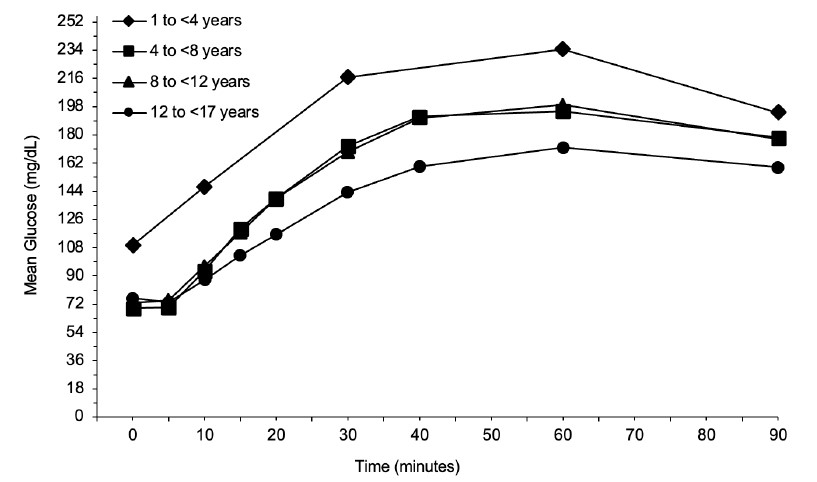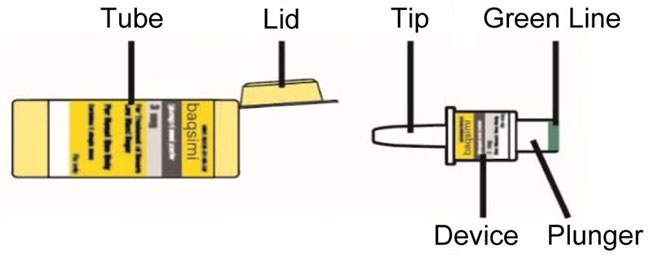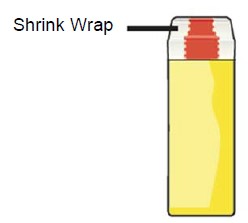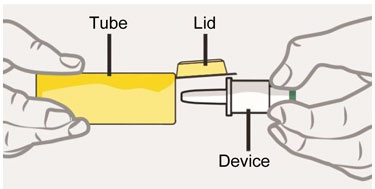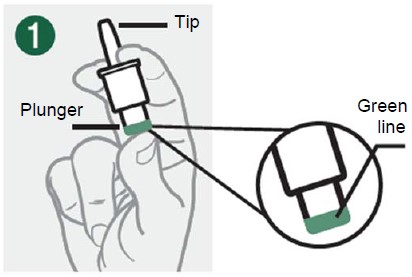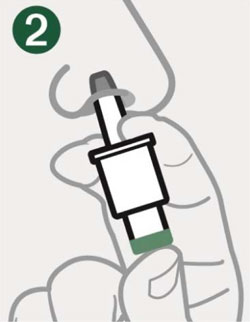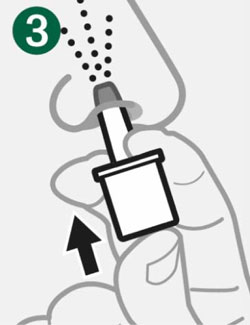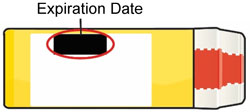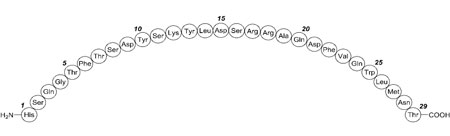 DRUG LABEL: Baqsimi
NDC: 0548-8351 | Form: POWDER
Manufacturer: Amphastar Pharmaceuticals, Inc.
Category: prescription | Type: HUMAN PRESCRIPTION DRUG LABEL
Date: 20250806

ACTIVE INGREDIENTS: glucagon 3 mg/1 1
INACTIVE INGREDIENTS: Betadex 24 mg/1 1; Dodecylphosphocholine 3 mg/1 1; Water; Acetic Acid

HIGHLIGHTS OF PRESCRIBING INFORMATION

These highlights do not include all the information needed to use BAQSIMI safely and effectively. See full prescribing information for BAQSIMI.
BAQSIMI (glucagon) nasal powder
Initial U.S. Approval: 1960

RECENT MAJOR CHANGES

Indications and Usage (1)……………………………………….03/2025

1 INDICATIONS AND USAGE

BAQSIMI® is an antihypoglycemic agent indicated for the treatment of severe hypoglycemia in adults and pediatric patients aged 1 year and older with diabetes. (1)

2 DOSAGE AND ADMINISTRATION

- BAQSIMI is for intranasal use only. (2.1)
- The recommended dose of BAQSIMI is 3 mg administered as one actuation of the intranasal device into one nostril. (2.2)
- Administer BAQSIMI according to the printed instructions on the shrink-wrapped tube label and the Instructions for Use. (2.1)
- Administer the dose by inserting the tip into one nostril and pressing the device plunger all the way in until the green line is no longer showing. The dose does not need to be inhaled. (2.1)
- Call for emergency assistance immediately after administering the dose. (2.1)
- When the patient responds to treatment, give oral carbohydrates. (2.1)
- Do not attempt to reuse BAQSIMI. Each BAQSIMI device contains one dose of glucagon and cannot be reused. Discard any unused portion. (2.1)
- If there has been no response after 15 minutes, an additional 3 mg dose may be administered while waiting for emergency assistance. (2.2)

3 DOSAGE FORMS AND STRENGTHS

Nasal powder: intranasal device containing one dose of glucagon 3 mg (3)

4 CONTRAINDICATIONS

- Pheochromocytoma (4)
- Insulinoma (4)
- Known hypersensitivity to glucagon or to any of the excipients (4)

5 WARNINGS AND PRECAUTIONS

- Substantial Increase in Blood Pressure in Patients with Pheochromocytoma: Contraindicated in patients with pheochromocytoma because BAQSIMI may stimulate the release of catecholamines from the tumor. (5.1)
- Hypoglycemia in Patients with Insulinoma: In patients with insulinoma, administration may produce an initial increase in blood glucose; however, BAQSIMI may stimulate exaggerated insulin release from an insulinoma and cause hypoglycemia. If a patient develops symptoms of hypoglycemia after a dose of BAQSIMI, give glucose orally or intravenously. (5.2)
- Serious Hypersensitivity Reactions: Serious hypersensitivity reactions have been reported and include generalized rash, and in some cases anaphylactic shock with breathing difficulties, and hypotension. (5.3)
- Lack of Efficacy in Patients with Decreased Hepatic Glycogen: BAQSIMI is effective in treating hypoglycemia only if sufficient hepatic glycogen is present. Patients in states of starvation, with adrenal insufficiency or chronic hypoglycemia may not have adequate levels of hepatic glycogen for BAQSIMI to be effective. Patients with these conditions should be treated with glucose. (5.4)

6 ADVERSE REACTIONS

Most common (≥10%) adverse reactions associated with BAQSIMI are nausea, vomiting, headache, upper respiratory tract irritation (i.e., rhinorrhea, nasal discomfort, nasal congestion, cough, and epistaxis), watery eyes, redness of eyes, itchy nose, throat and eyes. (6.1)

To report SUSPECTED ADVERSE REACTIONS, contact Amphastar Pharmaceuticals, Inc. at 1-800-423-4136 or FDA at 1-800-FDA-1088 or www.fda.gov/medwatch.

7 DRUG INTERACTIONS

- Beta-blockers: Patients taking beta-blockers may have a transient increase in pulse and blood pressure. (7.1)
- Indomethacin: In patients taking indomethacin BAQSIMI may lose its ability to raise glucose or may produce hypoglycemia. (7.2)
- Warfarin: BAQSIMI may increase the anticoagulant effect of warfarin. (7.3)

FULL PRESCRIBING INFORMATION

1 INDICATIONS AND USAGE

BAQSIMI™ is indicated for the treatment of severe hypoglycemia in adults and pediatric patients aged 1 year and older with diabetes.

2 DOSAGE AND ADMINISTRATION

2.1 Important Administration Instructions

BAQSIMI is for intranasal use only.

Instruct patients and their caregivers on the signs and symptoms of severe hypoglycemia. Because severe hypoglycemia requires help of others to recover, instruct the patient to inform those around them about BAQSIMI and its Instructions for Use. Administer BAQSIMI as soon as possible when severe hypoglycemia is recognized.

Instruct the patient or caregiver to read the Instructions for Use at the time they receive a prescription for BAQSIMI. Emphasize the following instructions to the patient or caregiver:

- Do not push the plunger or test the device prior to administration.
- Administer BAQSIMI according to the printed instructions on the shrink-wrapped tube label and the Instructions for Use.
- Administer the dose by inserting the tip into one nostril and pressing the device plunger all the way in until the green line is no longer showing. The dose does not need to be inhaled.
- Call for emergency assistance immediately after administering the dose.
- If there has been no response after 15 minutes, an additional dose of BAQSIMI may be administered while waiting for emergency assistance.
- When the patient responds to treatment, give oral carbohydrates to restore the liver glycogen and prevent recurrence of hypoglycemia.
- Do not attempt to reuse BAQSIMI. Each BAQSIMI device contains one dose of glucagon and cannot be reused. Discard any unused portion.

2.2 Dosage in Adults and Pediatric Patients Aged 1 Year and Older

The recommended dose of BAQSIMI is 3 mg administered as one actuation of the intranasal device into one nostril.

If there has been no response after 15 minutes, an additional 3 mg dose of BAQSIMI from a new device may be administered while waiting for emergency assistance.

3 DOSAGE FORMS AND STRENGTHS

Nasal Powder:

- 3 mg glucagon: as a white powder in an intranasal device containing one dose of glucagon

4 CONTRAINDICATIONS

BAQSIMI is contraindicated in patients with:

- Pheochromocytoma because of the risk of substantial increase in blood pressure [see Warnings and Precautions (5.1)]
- Insulinoma because of the risk of hypoglycemia [see Warnings and Precautions (5.2)]
- Prior hypersensitivity reaction to glucagon or to any of the excipients in BAQSIMI. Allergic reactions have been reported with glucagon and include anaphylactic shock with breathing difficulties and hypotension [see Warnings and Precautions (5.3)]

5 WARNINGS AND PRECAUTIONS

5.1 Substantial Increase in Blood Pressure in Patients with Pheochromocytoma

BAQSIMI is contraindicated in patients with pheochromocytoma because glucagon may stimulate release of catecholamines from the tumor [see Contraindications (4)]. If the patient develops a substantial increase in blood pressure and a previously undiagnosed pheochromocytoma is suspected, 5 to 10 mg of phentolamine mesylate, administered intravenously, has been shown to be effective in lowering blood pressure.

5.2 Hypoglycemia in Patients with Insulinoma

In patients with insulinoma, administration of glucagon may produce an initial increase in blood glucose; however, BAQSIMI administration may directly or indirectly (through an initial rise in blood glucose) stimulate exaggerated insulin release from an insulinoma and cause hypoglycemia. BAQSIMI is contraindicated in patients with insulinoma [see Contraindications (4)]. If a patient develops symptoms of hypoglycemia after a dose of BAQSIMI, give glucose orally or intravenously.

5.3 Serious Hypersensitivity Reactions

Serious hypersensitivity reactions have been reported with glucagon products, including generalized rash, and in some cases anaphylactic shock with breathing difficulties and hypotension. Discontinue BAQSIMI if symptoms of serious hypersensitivity reactions occur. Advise patients and/or caregivers to seek immediate medical attention if the patient experiences any symptoms of serious hypersensitivity reactions. BAQSIMI is contraindicated in patients with a prior hypersensitivity reaction [see Contraindications (4)].

5.4 Lack of Efficacy in Patients with Decreased Hepatic Glycogen

Patients with insufficient hepatic stores of glycogen may not respond to BAQSIMI for the treatment of severe hypoglycemia [see Clinical Pharmacology (12.2)]. Insufficient hepatic stores of glycogen may be present in conditions such as states of starvation or in patients with adrenal insufficiency or chronic hypoglycemia.

6 ADVERSE REACTIONS

The following clinically significant adverse reactions are described elsewhere in labeling:

- Substantial Increase in Blood Pressure in Patients with Pheochromocytoma [see Warnings and Precautions (5.1)].
- Hypoglycemia in Patients with Insulinoma [see Warnings and Precautions (5.2)].
- Serious Hypersensitivity Reactions [see Warnings and Precautions (5.3)].
- Lack of Efficacy in Patients with Decreased Hepatic Glycogen [see Warnings and Precautions (5.4)].

6.1 Clinical Trials Experience

Because clinical trials are conducted under widely varying conditions, adverse reaction rates observed in the clinical trials of BAQSIMI cannot be directly compared with rates in clinical trials of other drugs and may not reflect the rates observed in practice.

Adverse Reactions in Adult Patients

Two similarly designed comparator-controlled trials, Study 1 and Study 2, evaluated the safety of a single intranasal dose of BAQSIMI compared to a 1 mg dose of intra-muscular glucagon (IMG) in adult patients with diabetes [see Clinical Studies (14.1)].

Table 1 presents adverse reactions that occurred with BAQSIMI at an incidence of ≥2% in a pool of Study 1 and Study 2.

Table 1: Pooled Adverse Reactions (≥2%) in Adult Patients with Type 1 and Type 2 Diabetes in Study 1and Study 2
Adverse Reaction | BAQSIMI 3 mg (N=153) %
Nausea | 26
Headache | 18
Vomiting | 15
Upper Respiratory Tract Irritationa | 12
a Upper Respiratory Tract Irritation: rhinorrhea, nasal discomfort, nasal congestion, cough, and epistaxis.

Nasal and ocular symptoms with BAQSIMI were solicited through a patient questionnaire in Study 1 and 2 and these adverse reactions are presented in Table 2.

Table 2: Solicited Nasal and Non-Nasal Adverse Reactions in Adult Patients with Type 1 and Type 2 Diabetes Pooled from Study 1 and 2
Adverse Reactiona | BAQSIMI 3 mg (n=153) %
Adverse Reactiona | Any increase in symptom severitya
Watery eyes | 59
Nasal congestion | 43
Nasal itching | 39
Runny nose | 35
Redness of eyes | 25
Itchy eyes | 22
Sneezing | 20
Itching of throat | 12
Itching of ears | 3
a Patients were asked to report whether they have the symptom, as well as severity (mild, moderate, severe) at baseline, and after glucagon administration.

Adverse Reactions in Pediatric Patients Aged 1 Year and Above

A single dose of BAQSIMI was compared to weight-based doses of 0.5 mg or 1 mg of IMG in pediatric patients aged 4 to less than 17 years with type 1 diabetes in Study 3 [see Clinical Studies (14.2)].

Table 3 presents adverse reactions that occurred with BAQSIMI in pediatric patients at an incidence of ≥2% in Study 3.

Table 3: Adverse Reactions (≥2%) Occurring in Pediatric Patients Aged 4 to less than 17 Years with Type 1 Diabetes in Study 3
Adverse Reaction | BAQSIMI 3 mg (n=36) %
Vomiting | 31
Headache | 25
Nausea | 17
Upper Respiratory Tract Irritationa | 17
a Upper Respiratory Tract Irritation: nasal discomfort, nasal congestion, sneezing.

Nasal and ocular symptoms with BAQSIMI were solicited through a patient questionnaire in pediatric patients in Study 3 and these adverse reactions are presented in Table 4.

Table 4: Solicited Nasal and Non-Nasal Adverse Reactions in Pediatric Patients Aged 4 to less than 17 Years with Type 1 Diabetes in Study 3
Adverse Reactiona | BAQSIMI 3 mg (n=36) %
 | Any increase in symptom severitya
Watery eyes | 47
Nasal congestion | 42
Nasal itching | 28
Runny nose | 25
Sneezing | 19
Itchy eyes | 17
Redness of eyes | 14
Itching of throat | 3
Itching of ears | 3
a Subjects were asked to report whether they have the symptom, as well as severity (mild, moderate, severe) at baseline, and after glucagon administration.

The safety of a single 3 mg intranasal dose of BAQSIMI was assessed in an open-label study of 7 pediatric patients aged 1 to less than 4 years with type 1 diabetes mellitus [see Clinical Studies (14.2)]. The safety profile observed in this trial in pediatric patients was comparable to that observed in adults and pediatric patients aged 4 to less than 17 years [see Clinical Pharmacology (12.2, 12.3)].

Other Adverse Reactions in Adult and Pediatric Patients

Other observed adverse reactions with BAQSIMI-treated patients across clinical trials were, dysgeusia, pruritus, tachycardia, hypertension, and additional upper respiratory tract irritation events (nasal pruritus, throat irritation, and parosmia).

7 DRUG INTERACTIONS

7.1 Beta-blockers

Patients taking beta-blockers may have a transient increase in pulse and blood pressure when given BAQSIMI.

7.2 Indomethacin

In patients taking indomethacin, BAQSIMI may lose its ability to raise blood glucose or may even produce hypoglycemia.

7.3 Warfarin

BAQSIMI may increase the anticoagulant effect of warfarin.

8 USE IN SPECIFIC POPULATIONS

8.1 Pregnancy

Risk Summary

Available data from case reports and a small number of observational studies with glucagon use in pregnant women over decades of use have not identified a drug associated risk of major birth defects, miscarriage or adverse maternal or fetal outcomes. Multiple small studies have demonstrated a lack of transfer of pancreatic glucagon across the human placental barrier during early gestation. In a rat reproduction study, no embryofetal toxicity was observed with glucagon administered by injection during the period of organogenesis at doses representing up to 40 times the human dose, based on body surface area (mg/m^2) (see Data).

The estimated background risk of major birth defects and miscarriage for the indicated population is unknown. In the U.S. general population, the estimated background risk of major birth defects and miscarriage in clinically recognized pregnancies is 2-4% and 15-20%, respectively.

Data

Animal Data

In pregnant rats given animal sourced glucagon twice-daily by injection at doses up to 2 mg/kg (up to 40 times the human dose based on body surface area extrapolation, mg/m^2) during the period of organogenesis, there was no evidence of increased malformations or embryofetal lethality.

8.2 Lactation

Risk Summary

There is no information available on the presence of glucagon in human or animal milk, the effects of the drug on the breastfed infant, or the effects of the drug on milk production. However, glucagon is a peptide and would be expected to be broken down to its constituent amino acids in the infant's digestive tract and is therefore, unlikely to cause harm to an exposed infant.

8.4 Pediatric Use

The safety and effectiveness of BAQSIMI for the treatment of severe hypoglycemia in patients with diabetes have been established in pediatric patients aged 1 year and older. Use of BAQSIMI for this indication is supported by evidence from an adequate and well-controlled study in adults with type 1 diabetes mellitus [see Clinical Studies (14.1)], a study in 48 pediatric patients aged 4 to less than 17 years with type 1 diabetes mellitus [see Clinical Studies (14.2)], and additional pharmacokinetic and safety data from a study of seven pediatric patients aged 1 to less than 4 years with type 1 diabetes mellitus [see Adverse Reactions (6.1),Clinical Pharmacology (12.2, 12.3), and Clinical Studies (14.2)].

The safety and effectiveness of BAQSIMI have not been established in pediatric patients younger than 1 year of age.

8.5 Geriatric Use

Clinical studies of BAQSIMI did not include sufficient numbers of subjects aged 65 and over to determine whether they respond differently from younger adult patients.

10 OVERDOSAGE

If overdosage occurs, the patient may experience nausea, vomiting, inhibition of GI tract motility, increase in blood pressure and pulse rate. In case of suspected overdosing, serum potassium levels may decrease and should be monitored and corrected if needed. If the patient develops a dramatic increase in blood pressure, phentolamine mesylate has been shown to be effective in lowering blood pressure for the short time that control would be needed. In the event of an overdose of BAQSIMI, consider contacting the Poison Help line (1-800-222-1222) or a medical toxicologist for additional overdosage management recommendation.

11 DESCRIPTION

BAQSIMI contains glucagon, an antihypoglycemic agent used to treat severe hypoglycemia. Glucagon is a single-chain polypeptide containing 29 amino acid residues and has a molecular weight of 3483, and is identical to human glucagon.

Its molecular formula is C153H225N43O49S, with the following molecular structure:

BAQSIMI is a preservative-free, white powder for intranasal administration in an intranasal device containing one dose of 3 mg glucagon. BAQSIMI contains glucagon as the active ingredient and betadex, and dodecylphosphocholine as the excipients.

12 CLINICAL PHARMACOLOGY

12.1 Mechanism of Action

Glucagon increases blood glucose concentration by activating hepatic glucagon receptors, thereby stimulating glycogen breakdown and release of glucose from the liver. Hepatic stores of glycogen are necessary for glucagon to produce an antihypoglycemic effect.

12.2 Pharmacodynamics

After administration of BAQSIMI in adult patients with diabetes, the mean maximum glucose increase from baseline was 140 mg/dL (Figure 1).

In pediatric patients aged 1 to less than 17 years with type 1 diabetes, the mean maximum glucose increase from baseline was 132 mg/dL (1 to less than 4 years), 138 mg/dL (4 to less than 8 years), 133 mg/dL (8 to less than 12 years), and 102 mg/dL (12 to less than 17 years) (Figure 2).

Sex and body weight had no clinically meaningful effects on the pharmacodynamics of BAQSIMI.

Common cold with nasal congestion tested with or without use of decongestant did not impact pharmacodynamics of BAQSIMI.

Figure 1 Mean glucose concentration over time after glucagon dose in adult Type 1 Diabetes patientswith insulin-induced hypoglycemia.

Figure 2 Mean glucose concentration over time in pediatric Type 1 Diabetes patients administered BAQSIMI

12.3 Pharmacokinetics

Absorption

Glucagon absorption via the intranasal route, achieved mean peak plasma levels of 6130 pg/mL at around 15 minutes.

Distribution

The apparent volume of distribution was approximately 885 L.

Elimination

The median half-life was approximately 35 minutes.

Metabolism

Glucagon is known to be degraded in the liver, kidneys, and plasma.

Specific Populations

Pediatrics

In pediatric patients (aged 1 to less than 17 years), glucagon via the intranasal route, achieved mean peak plasma levels between 10 and 20 minutes. The median half-life was 21 to 31 minutes.

Patients with Colds

Common cold with nasal congestion did not impact the pharmacokinetics of BAQSIMI.

Drug Interaction Studies

Common cold with use of decongestant did not impact the pharmacokinetics of BAQSIMI.

12.6 Immunogenicity

The observed incidence of anti-drug antibodies (ADA) is highly dependent on the sensitivity and specificity of the assay. Differences in assay methods preclude meaningful comparisons of the incidence of ADA in the studies described below with the incidence of anti-drug antibodies in other studies, including those of glucagon or of other glucagon products.

In 3 clinical trials, 3/124 (2%) of BAQSIMI-treated patients had treatment-emergent ADAs as detected by an affinity capture elution (ACE) ligand-binding immunogenicity assay. No neutralizing antibodies were detected. Because of the low occurrence of ADA, the effect of these
antibodies on the pharmacokinetics, pharmacodynamics, and/or effectiveness of BAQSIMI is unknown.

13 NONCLINICAL TOXICOLOGY

13.1 Carcinogenesis, Mutagenesis, Impairment of Fertility

Long term studies in animals to evaluate carcinogenic potential have not been performed. Recombinant glucagon was positive in the bacterial Ames assay. It was determined that an increase in colony counts was related to technical difficulties in running this assay with peptides. Studies in rats have shown that glucagon does not cause impaired fertility.

14 CLINICAL STUDIES

14.1 Adult Patients with Type 1 or Type 2 Diabetes Mellitus

Study 1 (NCT03339453) was a randomized, multicenter, open-label, 2-period, crossover study in adult patients with type 1 diabetes. The efficacy of a single 3 mg dose of BAQSIMI was compared to a 1 mg dose of intra-muscular glucagon (IMG). Insulin was used to reduce blood glucose levels to <60 mg/dL. Seventy patients were enrolled, with a mean age of 41.7 years and a mean diabetes duration of 20.1 years. Twenty-seven (39%) were female.

The primary efficacy outcome measure was the proportion of patients achieving treatment success, which was defined as either an increase in blood glucose to ≥70 mg/dL or an increase of ≥20 mg/dL from glucose nadir within 30 minutes after receiving study glucagon, without receiving additional actions to increase the blood glucose level. Glucose nadir was defined as the minimum glucose measurement at the time of, or within 10 minutes, following glucagon administration.

The mean nadir blood glucose was 54.5 mg/dL for BAQSIMI and 55.8 mg/dL for IMG. BAQSIMI demonstrated non-inferiority to IMG in reversing insulin-induced hypoglycemia with 100% of BAQSIMI-treated patients and 100% of IMG-treated patients achieving treatment success. The mean time to treatment success was 11.6 and 9.9 minutes in the BAQSIMI and IMG 1 mg treatment groups, respectively.

Table 5: Adult Patients with Type 1 Diabetes Meeting Treatment Success and Other Glucose Criteria in Study 1

 | Type 1 Diabetes (N=66) a
 | BAQSIMI 3 mg | IMG 1 mg
Treatment Success – n (%) | 66 (100%) | 66 (100%)
Treatment Difference (2-sided 95% confidence limit) b, c | 0% (-2.9%, 2.9%)
Glucose criterion met – n (%)
(i) ≥70 mg/dL (ii) Increase by ≥20 mg/dL from nadir Both (i) and (ii) | 66 (100%) 66 (100%) 66 (100%) | 66 (100%) 66 (100%) 66 (100%)
a The Efficacy Analysis Population consisted of all patients who received both doses of the Study Drug with evaluable primary outcome.
b Difference calculated as (percentage with success in BAQSIMI) – (percentage with success in IMG).
c 2-sided 95% confidence interval (CI) of paired differences using a Wald-Min correction; non-inferiority margin = -10%.

Study 2 (NCT01994746) was a randomized, multicenter, open-label, 2-period, crossover study in adult patients with type 1 diabetes or type 2 diabetes. The efficacy of a single 3 mg dose of BAQSIMI was compared to a 1 mg dose of intra-muscular glucagon (IMG). Insulin was used to reduce blood glucose levels to the hypoglycemic range with a target blood glucose nadir of <50 mg/dL.

Study 2 enrolled 83 patients 18 to <65 years of age. The mean age of patients with type 1 diabetes (N=77) was 32.9 years and a mean diabetes duration of 18.1 years, and 45 (58%) patients were female. The mean age of patients with type 2 diabetes (N=6) was 47.8 years, with a mean diabetes duration of 18.8 years, and 4 (67%) patients were female.

The mean nadir blood glucose was 44.2 mg/dL for BAQSIMI and 47.2 mg/dL for IMG. BAQSIMI demonstrated non-inferiority to IMG in reversing insulin-induced hypoglycemia with 98.8% of BAQSIMI-treated patients and 100% of IMG-treated patients achieving treatment success within 30 minutes.

The mean time to treatment success was 15.9 and 12.1 minutes in the BAQSIMI and IMG 1 mg treatment groups, respectively.

Table 6: Adult Patients with Type 1 and Type 2 Diabetes Meeting Treatment Success and Other Glucose Criteria in Study 2
 | Type 1 and Type 2 Diabetes (N=80) a
 | BAQSIMI 3 mg | IMG 1 mg
Treatment Success – n (%) | 79 (98.8%) | 80 (100%)
Treatment Difference (2-sided 95% confidence limit) b,c | -1.3% (-4.6%, 2.2%)
Glucose criterion met – n (%) d
(i) ≥70 mg/dL | 77 (96%) | 79 (99%)
(ii) Increase by ≥20 mg/dL from nadir | 79 (99%) | 80 (100%)
Both (i) and (ii) | 77 (96%) | 79 (99%)
a The Efficacy Analysis Population consisted of all patients who received both doses of the Study Drug with evaluable primary outcome.
b Difference calculated as (percentage with success in BAQSIMI) – (percentage with success in IMG).
c 2-sided 95% confidence interval (CI) of paired differences using a Wald-Min correction; non-inferiority margin = -10%.
d Percentage based on number of patients.

14.2 Pediatric Patients Aged 1 to less than 17 Years with Type 1 Diabetes Mellitus

Study 3 (NCT01997411) was a randomized, multicenter, clinical study that assessed BAQSIMI compared to intra-muscular glucagon (IMG) in pediatric patients aged 4 to less than 17 years with type 1 diabetes. Insulin was used to reduce blood glucose levels, and glucagon was administered after glucose reached <80 mg/dL. Efficacy was assessed based on percentage of patients with a glucose increase of ≥20 mg/dL from glucose nadir within 30 minutes following BAQSIMI administration.

Forty-eight patients were enrolled and received at least one dose of study drug. The mean age in the Young Children cohort (4 to <8 years) was 6.5 years. In the Children cohort (8 to <12 years), mean age was 11.1 years and in the Adolescents cohort (12 to <17 years) mean age was 14.6 years. In all age cohorts, the population was predominantly male and white.

Across all age groups, all (100%) patients in both treatment arms achieved an increase in glucose ≥20 mg/dL from glucose nadir within 20 minutes of glucagon administration. The mean time to reach a glucose increase of ≥20 mg/dL for BAQSIMI and IMG for all age groups is shown in Table 7.

Table 7: Mean Time to Reach Glucose Increase of ≥20 mg/dL from Nadir in Pediatric Patients with Type 1 Diabetes in Study 3
Increase from Nadir | Mean Time Post-Glucagon Administration (minutes)
Increase from Nadir | Young Children (4 to <8 years old) |  | Children (8 to <12 years old) |  | Adolescents (12 to <17 years old)
Increase from Nadir | IMGa N=6 | BAQSIMI 3 mg N=12 | IMGa N=6 | BAQSIMI 3 mg N=12 | IMGa N=12 | BAQSIMI 3 mg N=12
≥20 mg/dL | 10.8 | 10.8 | 12.5 | 11.3 | 12.5 | 14.2
a 0.5 mg or 1 mg of IMG (based upon body weight)

Study 4 (NCT04992312) was a phase 1, open-label, multi-center study with a primary objective of assessing the safety and tolerability of a single 3 mg dose of BAQSIMI in pediatric participants aged 1 to less than 4 years with type 1 diabetes mellitus. Patients were recommended to fast overnight before the dosing visit on Day 1, to achieve the target range glucose of 70 to 140 mg/dL (3.9 to 7.8 mmol/L) at baseline. Efficacy was assessed based on the percentage of patients with a glucose increase of ≥20 mg/dL from baseline within 30 minutes following BAQSIMI administration.

Seven patients were enrolled in the study, all received the planned 3 mg dose of BAQSIMI and completed the study. The mean age of the patients enrolled in the study was 2.98 years, with ages ranging from 1.8 to 4 years old. There were 4 males and 3 females enrolled in the study, all who were white.

All (100%) patients achieved an increase in glucose ≥20 mg/dL from baseline within 30 minutes of BAQSIMI administration.

16 HOW SUPPLIED/STORAGE AND HANDLING

BAQSIMI is supplied as an intranasal device containing one 3 mg dose of glucagon as a preservative free, white powder.

- BAQSIMI One Pack carton contains 1 intranasal device (NDC 0548-8351-01)
- BAQSIMI Two Pack carton contains 2 intranasal devices (NDC 0548-8352-02)
- Store at temperatures up to 86°F (30°C) in the shrink wrapped tube provided.
- Keep BAQSIMI in the shrink wrapped tube until ready to use. If the tube has been opened, BAQSIMI may have been exposed to moisture and may not work as expected.
- Discard BAQSIMI and tube after use.

17 PATIENT COUNSELING INFORMATION

Advise the patient and family members or caregivers to read the FDA-approved patient labeling (Patient Information and Instructions for Use).

Recognition of Severe Hypoglycemia:

Inform patient and family members or caregivers on how to recognize the signs and symptoms of severe hypoglycemia and the risks of prolonged hypoglycemia.

Serious Hypersensitivity Reactions:

Inform patients that serious hypersensitivity reactions can occur with BAQSIMI. Advise patients to seek immediate medical attention if they experience any symptoms of serious hypersensitivity reactions [see Warnings and Precautions (5.3)].

Marketed by: Amphastar Pharmaceuticals, Inc. Rancho Cucamonga, CA 91730, USA.

Copyright© 2025, Amphastar Pharmaceuticals, Inc. All rights reserved.

698351AMD

PATIENT INFORMATION
BAQSIMI® (BAK-see-mee)
(glucagon) nasal powder

What is BAQSIMI?
BAQSIMI is a prescription medicine used to treat very low blood sugar (severe hypoglycemia) in people with diabetes ages 1 year and above.
It is not known if BAQSIMI is safe and effective in children under 1 year of age.

Do not use BAQSIMI if you:

- have a tumor in the gland on top of your kidneys (adrenal gland) called pheochromocytoma.
- have a tumor in your pancreas called insulinoma.
- have had an allergic reaction to glucagon, or any of the ingredients in BAQSIMI. See the end of this Patient Information leaflet for a complete list of ingredients in BAQSIMI.

Talk with your healthcare provider before taking this medicine if you have any of these conditions.

Before using BAQSIMI, tell your healthcare provider about all of your medical conditions, including if you:

- have adrenal gland problems.
- have a tumor in your pancreas.
- have not had food or water for a long time (prolonged fasting or starvation).
- have low blood sugar that does not go away (chronic hypoglycemia).
- are pregnant or plan to become pregnant. It is not known if BAQSIMI will harm your unborn baby.
- are breastfeeding or plan to breastfeed. It is not known if BAQSIMI passes into your breast milk. You and your healthcare provider should decide if you can use BAQSIMI while breastfeeding.

Tell your healthcare provider about all the medicines you take, including prescription and over-the-counter medicines, vitamins, and herbal supplements.

How should I use BAQSIMI?

- Read the detailed Instructions for Use that comes with BAQSIMI.
- Use BAQSIMI exactly how your healthcare provider tells you to use it.
- Make sure your caregiver and those around you know where you keep your BAQSIMI and how to use BAQSIMI the right way before you need their help.
- BAQSIMI contains only 1 dose of medicine and cannot be reused.
- BAQSIMI should be given in one side of your nose (nostril) but does not need to be inhaled.
- BAQSIMI will work even if you have a cold or are taking cold medicine.
- Act quickly. Having very low blood sugar for a period of time may be harmful.
- After giving BAQSIMI, the caregiver should call for emergency medical help right away.
- When you are able to safely swallow food or drink, your caregiver should give you a fast-acting source of sugar (such as a regular soft drink or fruit juice) and a long-acting source of sugar (such as crackers with cheese or peanut butter).
- If the person does not respond after 15 minutes, another dose of BAQSIMI from a new device may be given, if available while waiting for emergency services.
- Tell your healthcare provider each time you use BAQSIMI.

What are the possible side effects of BAQSIMI?
BAQSIMI may cause serious side effects, including:

- High blood pressure. BAQSIMI can cause high blood pressure in certain people with tumors in their adrenal glands.
- Low blood sugar. BAQSIMI can cause certain people with tumors in their pancreas called insulinomas to have low blood sugar.
- Serious allergic reaction. Call your healthcare provider or get medical help right away if you have a serious allergic reaction including:

- rash
- hives
- cough

- difficulty breathing
- trouble swallowing
- swelling of face, lips, or tongue

- low blood pressure
- feeling dizzy or faint
- fast heartbeat

The most common side effects of BAQSIMI include:

- nausea
- vomiting
- headache
- runny nose

- discomfort in your nose
- stuffy nose
- cough
- nose bleed

- watery eyes
- redness in your eyes
- itchy nose, throat, and eyes

These are not all the possible side effects of BAQSIMI. For more information, ask your healthcare provider.
Call your healthcare provider for medical advice about side effects. You may report side effects to the FDA at 1-800-FDA-1088.

How should I store BAQSIMI?

- Store BAQSIMI at temperatures up to 86ºF (30ºC).
- Keep BAQSIMI in the shrink wrapped tube until you are ready to use it.
- Throw away (discard) BAQSIMI and tube after use. Used BAQSIMI may be placed in household trash.

Keep BAQSIMI and all medicines out of the reach of children.

General Information about the safe and effective use of BAQSIMI.
Medicines are sometimes prescribed for purposes other than those listed in a Patient Information leaflet. Do not use BAQSIMI for a condition for which it was not prescribed. Do not give BAQSIMI to other people, even if they have the same symptoms that you have. It may harm them.
You can ask your pharmacist or healthcare provider for information about BAQSIMI that is written for health professionals.

What are the ingredients in BAQSIMI?
Active Ingredient: glucagon
Inactive Ingredients: betadex and dodecylphosphocholine

Marketed by: Amphastar Pharmaceuticals, Inc. Rancho Cucamonga, CA 91730, U.S.A.
www.baqsimi.com
Copyright © 2025, Amphastar Pharmaceuticals, Inc. All rights reserved.

For more information, call 1-800-423-4136 or go to the following website: www.baqsimi.com.

This Patient Information has been approved by the U.S. Food and Drug Administration

Issued: April, 2025

698351AMD

INSTRUCTIONS FOR USE

BAQSIMI®

(glucagon) nasal powder

3 mg

Read the Instructions for Use for BAQSIMI before using it. BAQSIMI is used to treat very low blood sugar (severe hypoglycemia) that will cause you to need help from others. You should make sure you show your caregivers, family and friends where you keep BAQSIMI and explain how to use it by sharing these instructions. They need to know how to use BAQSIMI before an emergency happens.

Tube and Device Parts

Important Information to Know

- Do not remove the Shrink Wrap or open the Tube until you are ready to use it.
- If the Tube has been opened, BAQSIMI could be exposed to moisture. This could cause BAQSIMI not to not work as expected.
- Do not push the plunger or test BAQSIMI before you are ready to use it.
- BAQSIMI contains 1 dose of glucagon nasal powder and cannot be reused.
- BAQSIMI is for nasal (nose) use only.
- BAQSIMI will work even if you have a cold or are taking cold medicine.

Preparing the Dose

Remove the Shrink Wrap by pulling on red stripe.

- Open the Lid and remove the Device from the Tube.
  Caution: Do not press the Plunger until ready to give the dose.

Giving the Dose

- Hold Device between fingers and thumb.
- Do not push Plunger yet.

- Insert Tip gently into one nostril until finger(s) touch the outside of the nose.

- Push Plunger firmly all the way in.
- Dose is complete when the Green Line disappears.

After giving BAQSIMI

- Call for emergency medical help right away.
- If the person is passed out (unconscious) turn the person on their side.
- Encourage the person to eat as soon as possible. When they can safely swallow, give the person a fast-acting source of sugar such as juice. Then encourage the person to eat a snack such as crackers with cheese or peanut butter.
- If the person does not respond after 15 minutes, another dose may be given, if available.

Storage and Handling

- Do not remove the Shrink Wrap or open the Tube until you are ready to use it.
- Store BAQSIMI in the shrink wrapped Tube at temperatures up to 86º F (30ºC).
- Throw away (discard) BAQSIMI and Tube after use. Used BAQSIMI may be placed in household trash.
- Caution: Replace the used BAQSIMI right away so you will have a new BAQSIMI in case you need it.
- Replace BAQSIMI before the expiration date printed on the Tube or carton.

- Keep BAQSIMI and all medicines out of the reach of children.

For Questions or More Information about BAQSIMI

- Call your healthcare provider
- Call Amphastar Pharmaceuticals, Inc. at 1-800-423-4136
- Visit www.baqsimi.com

BAQSIMI is a registered trademark of Amphastar Pharmaceuticals, Inc.

Marketed by: Amphastar Pharmaceuticals, Inc. Rancho Cucamonga, CA 91730, U.S.A

Copyright © 2025, Amphastar Pharmaceuticals, Inc.

BAQSIMI Device meets all applicable requirements defined in ISO 20072

This Instructions for Use has been approved by the U.S. Food and Drug Adminstration
Revised: March, 2025

678351AMC/3-25

PACKAGE LABEL – Baqsimi 3 mg Nasal Powder One Pack

NDC 0548-8351-01

baqsimi®

(glucagon) nasal powder

3 mg

For Treatment of Severe Low Blood Sugar

For Nasal Use Only

Contains 1 nasal device.

Keep tube sealed until ready to use.

Rx only

BAQSIMI One Pack®

www.baqsimi.com

568351AMA/5-23

PACKAGE LABEL – Baqsimi 3 mg Nasal Powder Two Pack

NDC 0548-8352-02

baqsimi®

(glucagon) nasal powder

3 mg

For Treatment of Severe Low Blood Sugar

For Nasal Use Only

Contains 2 nasal devices.

Keep tubes sealed until ready to use.

Rx only

BAQSIMI Two Pack®

www.baqsimi.com

528352AMA/5-23